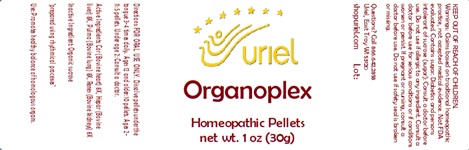 DRUG LABEL: Organoplex
NDC: 48951-7095 | Form: PELLET
Manufacturer: Uriel Pharmacy Inc.
Category: homeopathic | Type: HUMAN OTC DRUG LABEL
Date: 20240513

ACTIVE INGREDIENTS: BEEF HEART 8 [hp_X]/1 1; MAMMAL LIVER 8 [hp_X]/1 1; SUS SCROFA LUNG 8 [hp_X]/1 1; PORK KIDNEY 8 [hp_X]/1 1
INACTIVE INGREDIENTS: SUCROSE

Organoplex

INDICATIONS AND USAGE

Directions: FOR ORAL USE ONLY.

DOSAGE AND ADMINISTRATION

Dissolve pellets under the tongue 3-4 times daily. Ages 12 and older: 10 pellets. Ages 2-11: 5 pellets. Under age 2: Consult a doctor.

ACTIVE INGREDIENT

Active Ingredients: Cor (Bovine heart) 8X, Hepar (Bovine liver) 8X, Pulmo (Bovine lung) 8X, Renes (Bovine kidneys) 8X

Inactive Ingredients: Organic sucrose

"prepared using rhythmical processes"

PURPOSE

Use: Promotes healthy balance of homologous organs.

KEEP OUT OF REACH OF CHILDREN.

WARNINGS

Warnings: Claims based on traditional homeopathic practice, not accepted medical evidence. Not FDA evaluated. Contains sugar. Diabetics and persons intolerant of sucrose (sugar): Consult a doctor before use. Do not use if allergic to any ingredient. Consult a doctor before use for serious conditions or if conditions worsen or persist. If pregnant or nursing, consult a doctor before use. Do not use if safety seal is broken or missing.

QUESTIONS

Questions? Call 866.642.2858 Uriel, East Troy, WI 53120 shopuriel.com Lot: